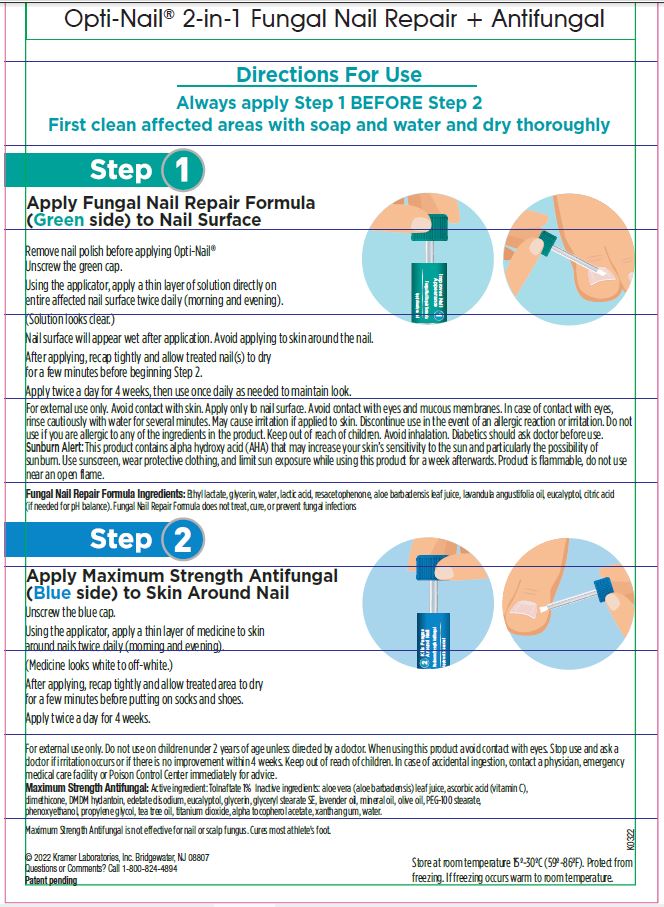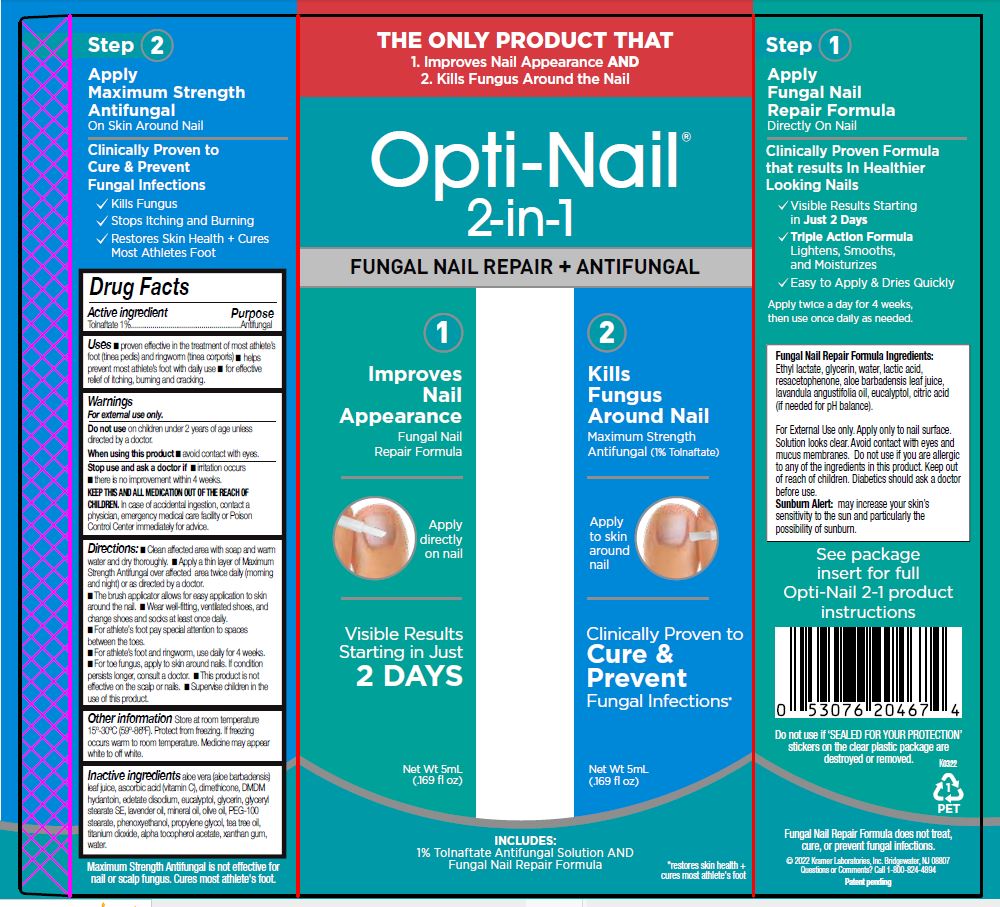 DRUG LABEL: Opti-Nail 2-in-1
NDC: 55505-219 | Form: LIQUID
Manufacturer: Kramer Laboratories
Category: otc | Type: HUMAN OTC DRUG LABEL
Date: 20251223

ACTIVE INGREDIENTS: Tolnaftate 1 g/100 mL
INACTIVE INGREDIENTS: Aloe Vera Leaf; Ascorbic Acid; Dimethicone; Dmdm Hydantoin; Edetate Disodium; Eucalyptol; Glycerin; Glyceryl Stearate Se; Lavender Oil; Mineral Oil; Olive Oil; Peg-100 Stearate; Phenoxyethanol; Propylene Glycol; Tea Tree Oil; Titanium Dioxide; .Alpha.-Tocopherol Acetate; Xanthan Gum; Water

Drug facts

Active ingredient | Purpose
Tolnaftate 1% | Anti-fungal

Uses

- proven effective in the treatment of most athlete’s foot (tinea pedis) and ringworm (tinea corporis)
- helps prevent most athlete’s foot with daily use
- for effective relief of itching, burning and cracking.

Warnings

For external use only.

Do not use on children under 2 years of age unless directed by a doctor.

When using this product

- avoid contact with eyes.

Stop use and ask a doctor if

- irritation occurs
- there is no improvement within 4 weeks.

KEEP THIS AND ALL MEDICATION OUT OF THE REACH OF CHILDREN.

In case of accidental ingestion, contact a physician, emergency medical care facility or Poison Control Center immediately for advice.

Directions:

- Clean affected area with soap and warm water and dry thoroughly.
- Apply a thin layer of Maximum Strength Antifungal over affected area twice daily (morning and night) or as directed by a doctor.
- The brush applicator allows for easy application to skin around the nail.
- Wear well-fitting, ventilated shoes, and change shoes and socks at least once daily.
- For athlete’s foot pay special attention to spaces between the toes.
- For athlete’s foot and ringworm, use daily for 4 weeks.
- For toe fungus, apply to skin around nails. If condition persists longer, consult a doctor.
- This product is not effective on the scalp or nails.
- Supervise children in the use of this product.

Other information

Store at room temperature 15º−30ºC (59º−86ºF).

Inactive ingredients

aloe vera (aloe barbadensis) gel, ascorbic acid (vitamin C), dimethicone, DMDM hydantoin, edetate disodium dihydrate, eucalyptol, glycerin, glyceryl stearate SE, lavender oil, mineral oil, olive oil, PEG-100 stearate, phenoxetol, propylene glycol, tea tree oil, titanium dioxide, alpha tocopheryl acetate (vitamin E), xanthan gum, water

PACKAGE LABEL

THE ONLY PRODUCT THAT
1. Improves Nail Appearance AND
2. Kills Fungus Around the Nail
NEW
Opti-Nail™
2-in-1
FUNGAL NAIL REPAIR + ANTI-FUNGAL
1
Improves Nail Appearance
Fungal Nail Repair Formula
Apply directly on nail
Visible Results Starting in Just 2 DAYS
Net Wt 5mL
(.169 fl oz)
2
Kills Fungus Around Nail
Maximum Strength Antifungal (1% Tolnaftate)
Apply to skin around nail
Clinically Proven to
Cure & Prevent
Fungal Infections*
Net Wt 5mL
(.169 fl oz)
INCLUDES:
1% Tolnaftate Antifungal Solution AND Fungal Nail Repair Formula
*restores skin health + cures most athlete's foot
Step 1
Apply Fungal Nail Repair Formula
Directly On Nail
Clinically Proven Formula that results In Healthier Looking Nails
✓ Visible Results Starting in Just 2 Days
✓ Triple Action Formula Lightens, Smooths, and Moisturizes
✓ Easy to Apply & Dries Quickly
Apply twice a day for 4 weeks, then use once daily as needed.
Fungal Nail Repair Formula Ingredients:
Ethyl lactate, glycerin, water, lactic acid, resacetophenone, citric acid (if needed for pH balance).
For External Use only. Apply only to nail surface.
Avoid contact with eyes and mucus membranes.
Do not use if you are allergic to any of the ingredients in this product.
Keep out of reach of children.
Diabetics should ask a doctor before use.
Sunburn Alert: may increase your skin's sensitivity to the sun and particularly the possibility of sunburn.
See package insert for full Opti-Nail 2-1 product instructions
Do not use if neck band is missing or broken
K0322
Fungal Nail Repair Formula does not treat, cure, or prevent fungal infections.
© 2022 Kramer Laboratories, Inc. Bridgewater, NJ 08807
Questions or Comments? Call 1-800-824-4894
Patent pending
Step 2
Apply Maximum Strength Antifungal
On Skin Around Nail
Clinically Proven to
Cure & Prevent
Fungal Infections
✓ Kills Fungus
✓ Stops Itching and Burning
✓ Restores Skin Health + Cures Most Athletes Foot
Maximum Strength Anti-Fungal not for nail or scalp fungus. Cures most athlete's foot.

Opti-Nail™ 2-in-1 Fungal Nail Repair + Antifungal
Directions For Use
Always apply step 1 BEFORE Step 2
First clean affected areas with soap and water and dry thoroughly
Step 1
Apply Fungal Nail Repair Formula
(Green side) to Nail Surface
Unscrew the green cap.
Using the applicator, apply a thin layer of solution directly on entire affected nail surface twice daily (morning and evening).
(Solution looks clear.)
Nail surface will appear wet after application. Avoid applying to skin around the nail.
After applying, recap tightly and allow treated nails(s) to dry for a few minutes before beginning Step 2.
Apply twice a day for 4 weeks, then use once daily as needed to maintain look.
For external use only. Avoid contact with skin. Apply only to nail surface. Avoid contact with eyes and mucous membranes. In case of contact with eyes, rinse cautiously with water for several minutes. May cause irritation if applied to skin. Discontinue use in the event of an allergic reaction or irritation. Do not use if you are allergic to any of the ingredients in the product. Keep out of reach of children. Avoid inhalation. Diabetics should ask doctor before use.
Sunburn Alert: This product contains alpha hydroxy acid (AHA) that may increase your skin's sensitivity to the sun and particularly the possibility of sunburn. Use sunscreen, wear protective clothing, and limit sun exposure while using this product for a week afterwards. Product is flammable, do not use near an open flame.
Fungal Nail Repair Formula Ingredients: Ethyl lactate, glycerin, water, lactic acid, resacetophenone, citric acid (if needed for pH balance).
Fungal Nail Repair Formula does not treat, cure, or prevent fungal infections
Step 2
Apply Maximum Strength Antifungal
(Blue side) to Skin Around Nail
Unscrew the blue cap.
Using the applicator, apply a thin layer of medicine to skin around nails twice daily (morning and evening).
(Medicine looks white to off-white.)
After applying, recap tightly and allow treated area to dry for a few minutes before putting on socks and shoes.
Apply twice a day for 4 weeks.
For external use only. Do not use on children under 2 years of age unless directed by a doctor. When using this product avoid contact with eyes. Stop use and ask a doctor if irritation occurs of it there is no improvement within 4 weeks. Keep out of reach of children. In case of accidental ingestion, contact a physician, emergency medical care facility or Poison Control Center immediately for advice.
Maximum Strength Antifungal: Active ingredient: Tolnaftate 1% Inactive ingredients: aloe vera (aloe barbadensis) gel, ascorbic acid (vitamin C), dimethicone, DMDM hydantoin, edetate disodium dihydrate, eucalyptol, glycerin, glyceryl stearate SE, lavender oil, mineral oil, olive oil, PEG-100 stearate, phenoxetol, propylene glycol, tea tree oil, titanium dioxide, tocopheryl acetate (vitamin E), xanthan gum, water
Maximum Strength Antifungal is not effective for nail or scalp fungus. Cures most athlete's foot.
©2022 Kramer Laboratories, Inc. Bridgewater, NJ 08807
Questions or Comments? Call 1-800-824-4894
Patent pending
Store at room temperature 15°−30°C (59°−86°F)
K0322